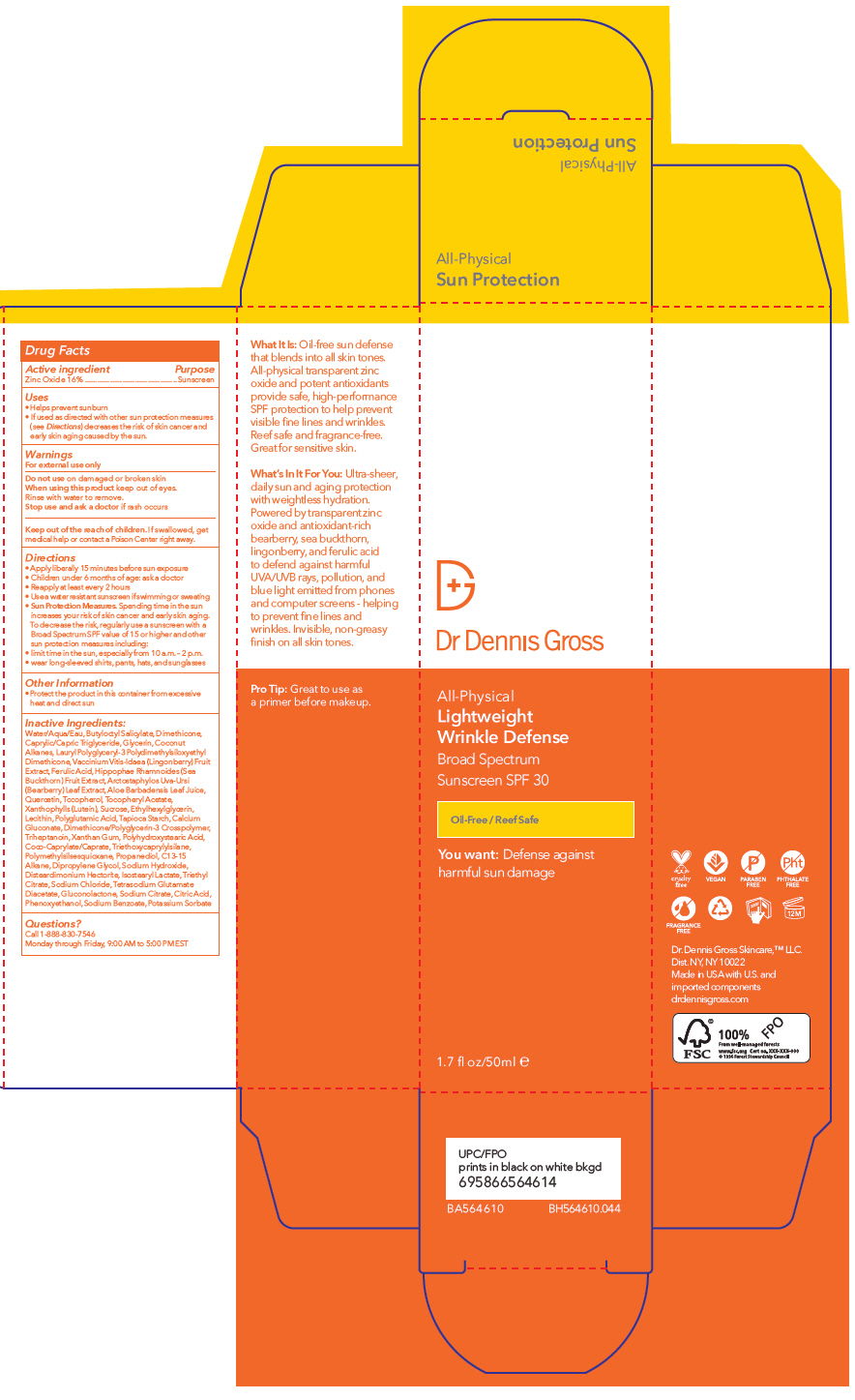 DRUG LABEL: Dr. Dennis Gross Skincare - Lightweight Wrinkle Defense Broad Spectrum SPF 30
NDC: 66163-4272 | Form: LIQUID
Manufacturer: Cosmetic Solutions LLC
Category: otc | Type: HUMAN OTC DRUG LABEL
Date: 20230119

ACTIVE INGREDIENTS: Zinc Oxide 16 g/100 mL
INACTIVE INGREDIENTS: Water; Butyloctyl Salicylate; Dimethicone; Medium-Chain Triglycerides; Glycerin; Coconut Alkanes; Lingonberry; Ferulic Acid; Aloe Vera Leaf; Quercetin; Tocopherol; .Alpha.-Tocopherol Acetate; Lutein; Starch, Tapioca; Calcium Gluconate; Triheptanoin; Xanthan Gum; Cocoyl Caprylocaprate; Triethoxycaprylylsilane; Polymethylsilsesquioxane (4.5 Microns); Propanediol; C13-15 Alkane; Dipropylene Glycol; Sodium Hydroxide; Disteardimonium Hectorite; Isostearyl Lactate; Triethyl Citrate; Sodium Chloride; Tetrasodium Glutamate Diacetate; Gluconolactone; Sodium Citrate, Unspecified Form; Citric Acid Monohydrate; Phenoxyethanol; Sodium Benzoate; Potassium Sorbate

Dr. Dennis Gross Skincare - Lightweight Wrinkle Defense Broad Spectrum SPF 30

Drug Facts

Active ingredient

Zinc Oxide 16%

Purpose

Sunscreen

Uses

- Helps prevent sunburn
- If used as directed with other sun protection measures (see Directions) decreases the risk of skin cancer and early skin aging caused by the sun.

Warnings

For external use only

Do not use on damaged or broken skin

When using this product keep out of eyes. Rinse with water to remove.

Stop use and ask a doctor if rash occurs

KEEP OUT OF REACH OF CHILDREN

Keep out of the reach of children. If swallowed, get medical help or contact a Poison Center right away.

Directions

- Apply liberally 15 minutes before sun exposure
- Children under 6 months of age: ask a doctor
- Reapply at least every 2 hours
- Use a water resistant sunscreen if swimming or sweating
- Sun Protection Measures. Spending time in the sun increases your risk of skin cancer and early skin aging. To decrease the risk, regularly use a sunscreen with a Broad Spectrum SPF value of 15 or higher and other sun protection measures including:
  - limit time in the sun, especially from 10 a.m. – 2 p.m.
  - wear long-sleeved shirts, pants, hats, and sunglasses

Other Information

- Protect the product in this container from excessive heat and direct sun

Inactive Ingredients

Water/Aqua/Eau, Butyloctyl Salicylate, Dimethicone, Caprylic/Capric Triglyceride, Glycerin, Coconut Alkanes, Lauryl Polyglyceryl-3 Polydimethylsiloxyethyl Dimethicone, Vaccinium Vitis-Idaea (Lingonberry) Fruit Extract, Ferulic Acid, Hippophae Rhamnoides (Sea Buckthorn) Fruit Extract, Arctostaphylos Uva-Ursi (Bearberry) Leaf Extract, Aloe Barbadensis Leaf Juice, Quercetin, Tocopherol, Tocopheryl Acetate, Xanthophylls (Lutein), Sucrose, Ethylhexylglycerin, Lecithin, Polyglutamic Acid, Tapioca Starch, Calcium Gluconate, Dimethicone/Polyglycerin-3 Crosspolymer, Triheptanoin, Xanthan Gum, Polyhydroxystearic Acid, Coco-Caprylate/Caprate, Triethoxycaprylylsilane, Polymethylsilsesquioxane, Propanediol, C13-15 Alkane, Dipropylene Glycol, Sodium Hydroxide, Disteardimonium Hectorite, Isostearyl Lactate, Triethyl Citrate, Sodium Chloride, Tetrasodium Glutamate Diacetate, Gluconolactone, Sodium Citrate, Citric Acid, Phenoxyethanol, Sodium Benzoate, Potassium Sorbate

Questions?

Call 1-888-830-7546
Monday through Friday, 9:00 AM to 5:00 PM EST

PRINCIPAL DISPLAY PANEL - 50 ml Tube Carton

Dr Dennis Gross

All-Physical

Lightweight
Wrinkle Defense

Broad Spectrum
Sunscreen SPF 30

Oil-Free / Reef Safe

You want: Defense against
harmful sun damage

1.7 fl oz/50ml ℮